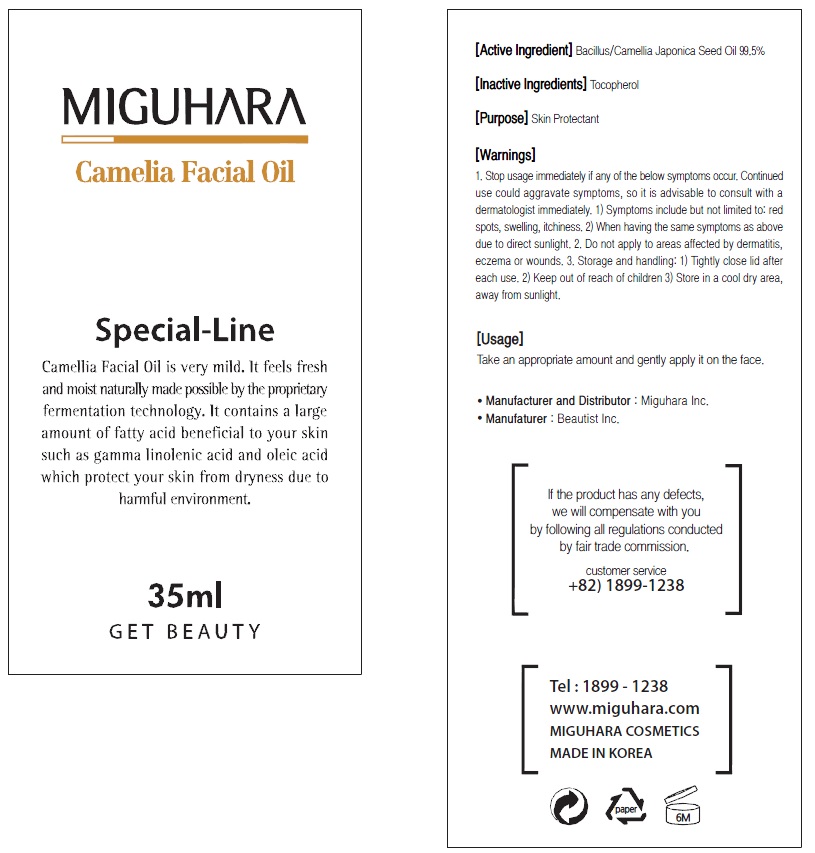 DRUG LABEL: Camelia Facial
NDC: 70380-150 | Form: OIL
Manufacturer: MIGUHARA
Category: otc | Type: HUMAN OTC DRUG LABEL
Date: 20160222

ACTIVE INGREDIENTS: CAMELLIA JAPONICA SEED OIL 34.8 g/35 mL
INACTIVE INGREDIENTS: Tocopherol

ACTIVE INGREDIENT

Active Ingredient: Bacillus/Camellia Japonica Seed Oil 99.5%

INACTIVE INGREDIENT

Inactive Ingredients: Tocopherol

PURPOSE

Purpose: Skin Protectant

WARNINGS

1) Symptoms include but not limited to: red spots, swelling, itchiness. 2) When having the same symptoms as above due to direct sunlight. 2. Do not apply to areas affected by dermatitis, eczema or wounds. 3. Storage and handling: 1) Tightly close lid after each use. 2 Keep out of reach of children 3) Store in a cool dry area, away from sunlight

KEEP OUT OF REACH OF CHILDREN

Usage

Usage: Take an appropriate amount and gently apply it on the face.

Usage

Usage: Take an appropriate amount and gently apply it on the face.